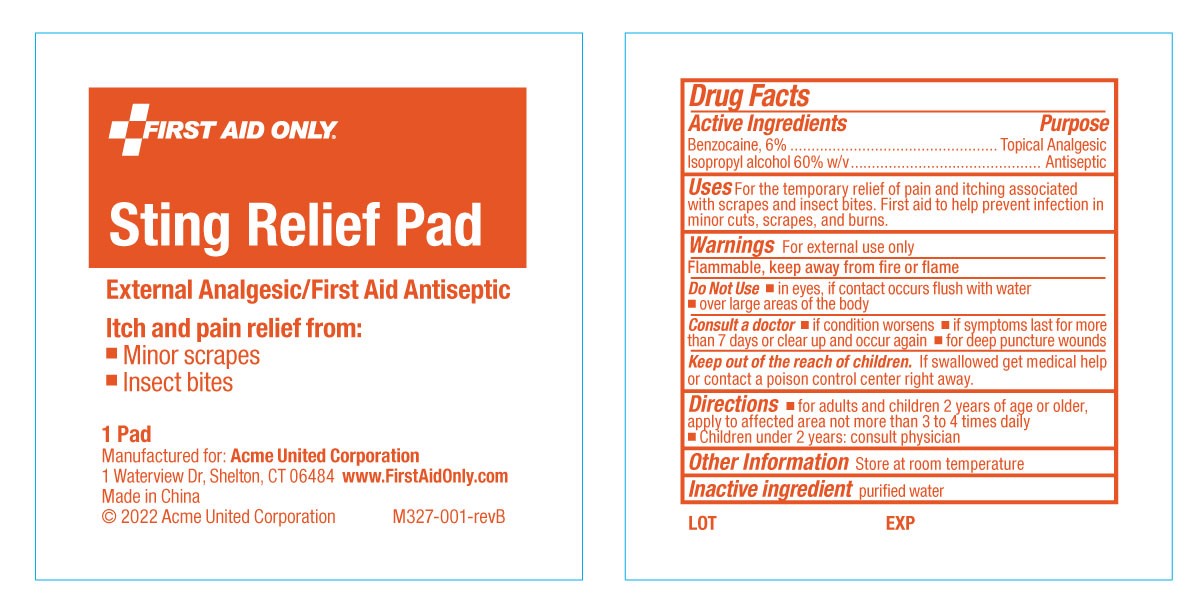 DRUG LABEL: First Aid Only Sting Relief Pad
NDC: 0924-5204 | Form: LIQUID
Manufacturer: Acme United Corporation
Category: otc | Type: HUMAN OTC DRUG LABEL
Date: 20241126

ACTIVE INGREDIENTS: BENZOCAINE 60 mg/1 mL; ISOPROPYL ALCOHOL 600 mg/1 mL
INACTIVE INGREDIENTS: WATER

First Aid Only Sting Relief Pad

Active ingredients

Benzocaine 6.0%

Isopropyl Alcohol 60% w/v

Purpose

Topical Anesthetic

Antiseptic

INDICATIONS AND USAGE

For the temporary relief of pain and itching associated with minor scrapes and insect bites.

First aid to help prevent infection in minor cuts, scrapes, and burns.

Warnings

For external use only

Flammable, keep away from fire or flame

Do Not Use

- in eyes, if contact occurs flush with water ▪over large areas of the body

ASK DOCTOR

Consult a doctor ▪if condition worsens ▪if symptoms last for more than seven days or clear up and occur again ▪for deep puncture wounds

Keep out of reach of children.

If swallowed, get medical help or contact a Poison Control center right away.

Directions

▪ For adults and children 2 years of age and older, apply to affected area not more than 3 to 4 times daily

▪Children under 2 years: consult physician

Inactive ingredient

Purified Water

Other information store at room temperature

pouch label